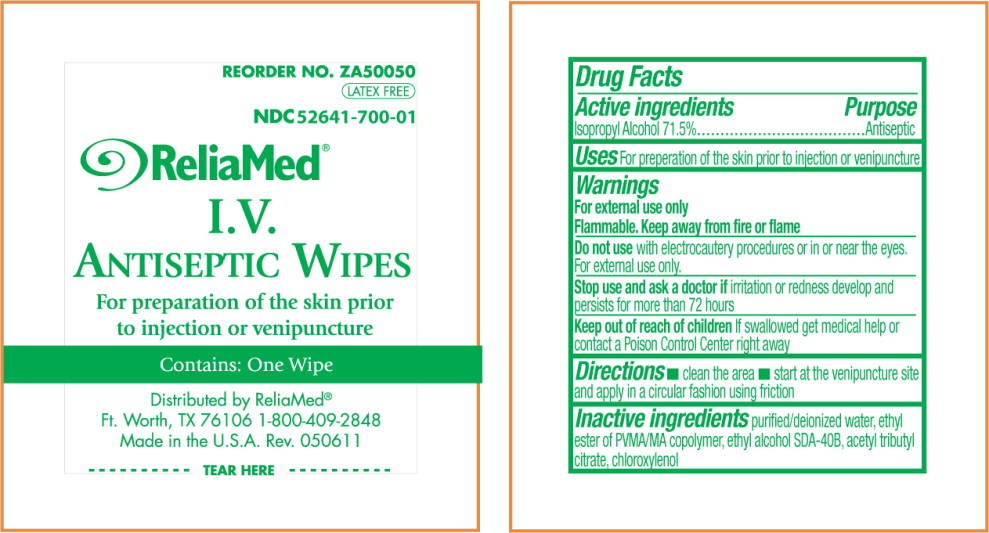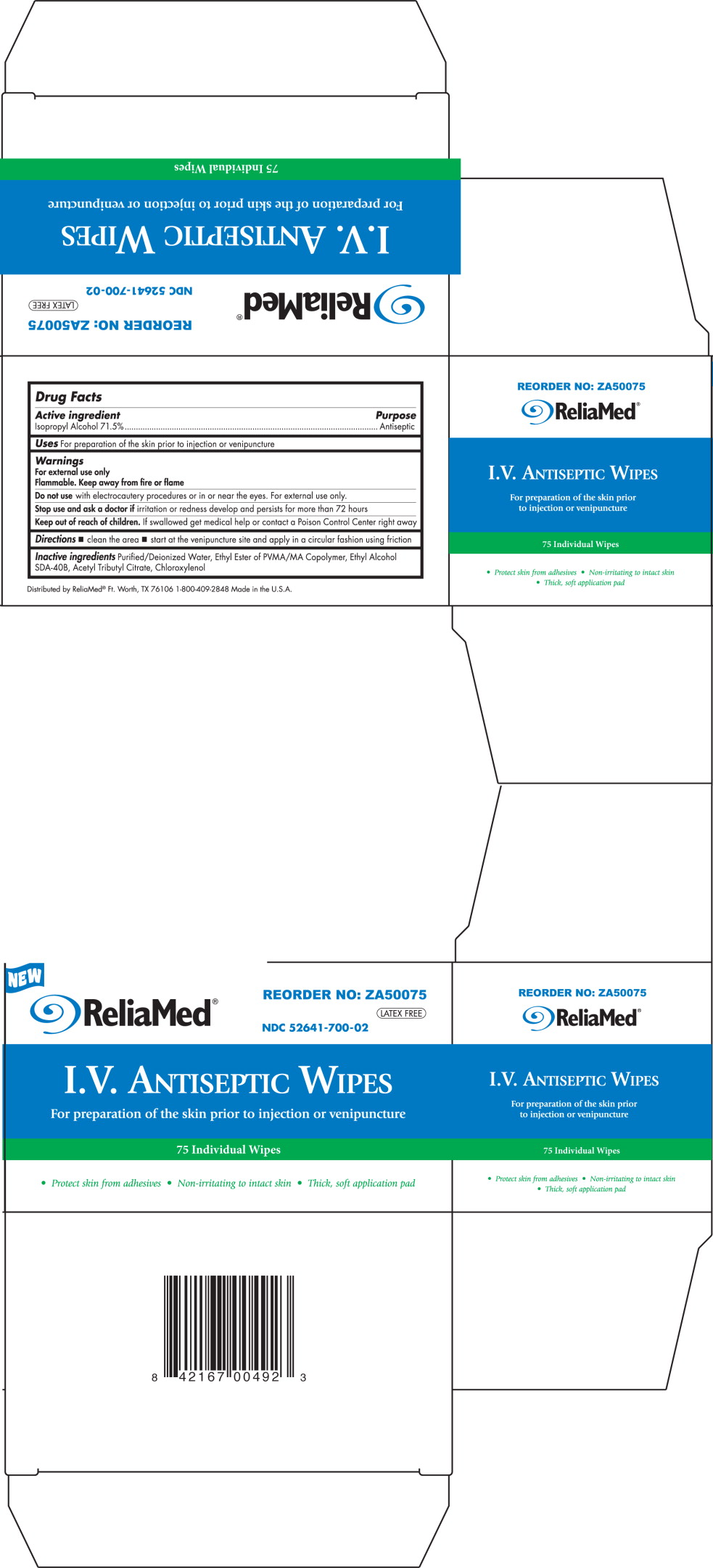 DRUG LABEL: Antiseptic
NDC: 52641-700 | Form: LIQUID
Manufacturer: ReliaMed
Category: otc | Type: HUMAN OTC DRUG LABEL
Date: 20130610

ACTIVE INGREDIENTS: isopropyl alcohol 0.56118 g/1 mL
INACTIVE INGREDIENTS: water; alcohol; acetyltributyl citrate; chloroxylenol; ethyl nitrate

Drug Facts

Active Ingredients

Isopropyl Alcohol 71.5%

Purpose

Antiseptic

Uses

For preparation of the skin prior to injection or venipuncture

Warnings

For external use only.

Flammable. Keep away from fire or flame.

Do not use with electrocautery procedures or in or near the eyes. For external use only.

Stop use and ask a doctor if irritation or redness develop and persists for more than 72 hours

Keep out of reach of children If swallowed, get medical help or contact a Poison Control Center right away.

Directions

- clean the area
- start at the venipuncture site and apply in a circular fashion using friction

Inactive ingredients

purified/deionized water, ethyl ester of PVMA/MA copolymer, ethyl alcohol SDA-40B, acetyl tributyl citrate, chloroxylenol

PRINCIPAL DISPLAY PANEL – packet label

REORDER NO. ZA50075

LATEX FREE

NDC 52641-700-02

ReliaMed

I.V.
Antiseptic Wipes
For preparation of the skin prior
to injection or venipuncture

Contains: One Wipe

Distributed by ReliaMed

Ft. Worth, TX 76106 1-800-409-2848

Made in the U.S.A. Rev 050611

TEAR HERE

PRINCIPAL DISPLAY PANEL – box label

NEW

ReliaMed

REORDER NO. ZA50075

LATEX FREE

NDC 52641-700-02

I.V. Antiseptic Wipes
For preparation of the skin prior to injection or venipuncture

75 Individual Wipes

- Protect skin from adhesives
- Non-irritating to intact skin
- Thick, soft application pad